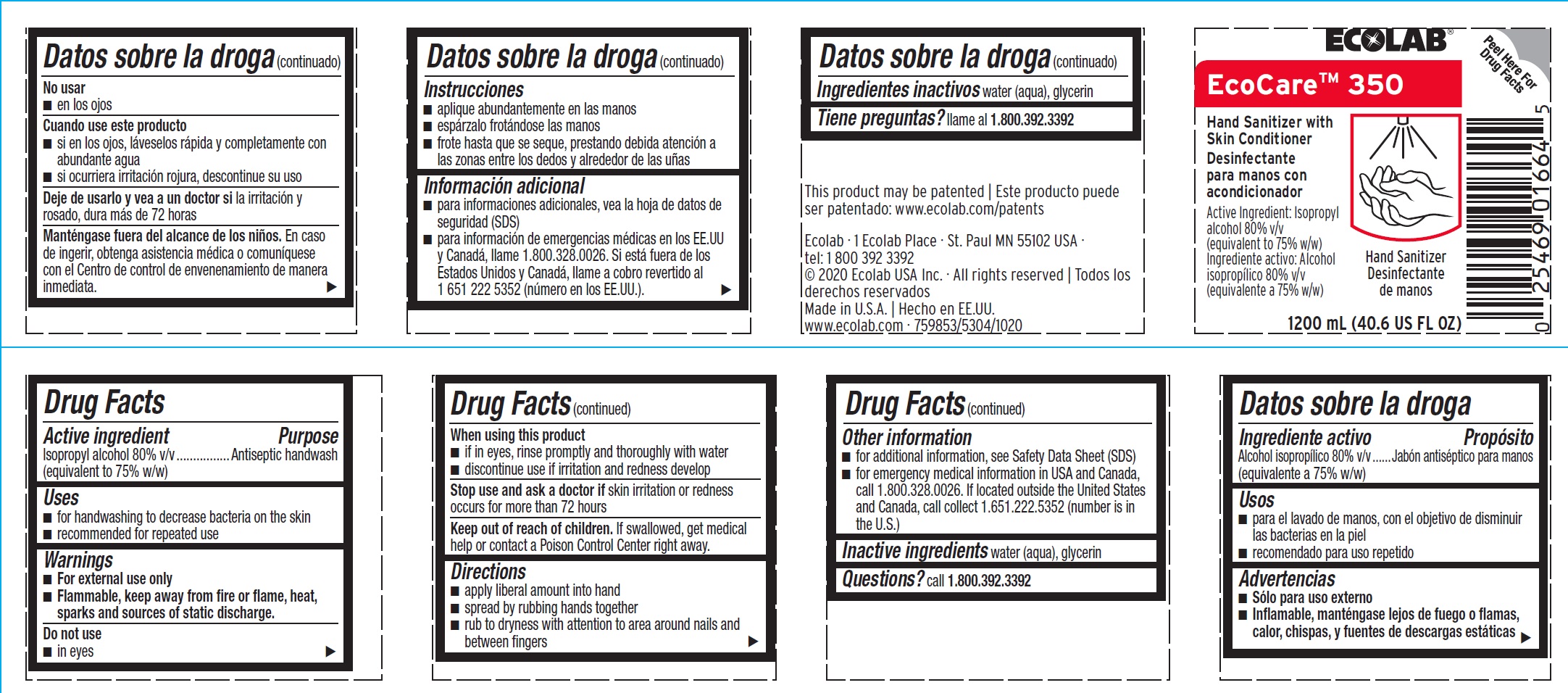 DRUG LABEL: EcoCare 350
NDC: 47593-363 | Form: SOLUTION
Manufacturer: Ecolab Inc.
Category: otc | Type: HUMAN OTC DRUG LABEL
Date: 20251010

ACTIVE INGREDIENTS: Isopropyl Alcohol 80 mL/100 mL
INACTIVE INGREDIENTS: WATER; GLYCERIN

Drug Facts

Active ingredient

Isopropyl alcohol 80% v/v (equivalent to 75% w/w)

Purpose

Antiseptic handwash

Uses

- for handwashing to decrease bacteria on the skin
- recommended for repeated use

Warnings

For external use only
Flammable, keep away from fire or flame, heat, sparks and sources of static discharge

Do not use

- in eyes

When using this product

- if in eyes, rinse promptly and thoroughly with water
- Discontinue use if irritation and redness develop

Stop use and ask a doctor if

- skin irritation or redness persists for more than 72 hours

Keep out of reach of children. If swallowed, get medical help or contact a Poison Control Center right away.

Directions

- apply liberal amount into hand
- spread by rubbing hands together
- rub to dryness with attention to area around nails and between fingers

Other information

- for additional information, see Safety Data Sheet (SDS)
- for emergency medical information in USA and Canada, call 1.800.328.0026. If located outside the United States and Canada, call collect 1.651.222.5352 (number is in the U.S.)

Inactive ingredients water (aqua), glycerin

Questions? call 1-800.392.3392

Principal Display Panel/Representative Label

ECOLAB®

EcoCare™ 350

Hand Sanitizer with Skin Conditioner

Active Ingredient:

Isopropyl alcohol 80% v/v

(equivalent to 75% w/w)

1200mL (40.6 US FL OZ)

This product may be patented

www.ecolab.com/patents

Ecolab · 1 Ecolab Place · St Paul MN 55102 USA · tel: 1 800 392 3392

© 2020 Ecolab USA Inc · All rights reserved

Made in U.S.A.

www.ecolab.com · 759853/5304/1020